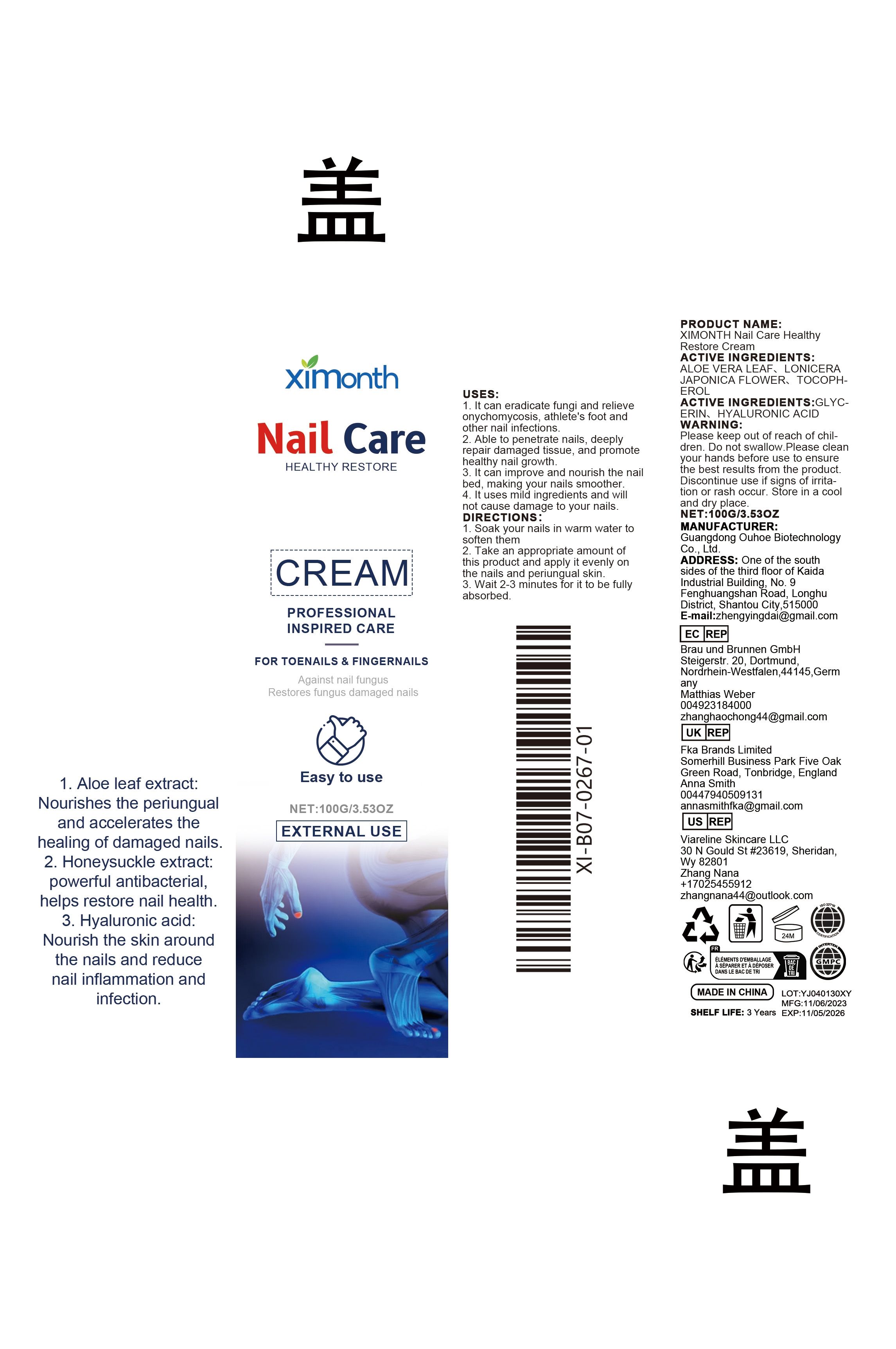 DRUG LABEL: XIMONTH Nail Care Healthy Restore Cream
NDC: 84744-007 | Form: CREAM
Manufacturer: Guangdong Ouhoe Biotechnology Co., Ltd.
Category: otc | Type: HUMAN OTC DRUG LABEL
Date: 20241105

ACTIVE INGREDIENTS: ALOE VERA LEAF 30 g/100 g; LONICERA JAPONICA FLOWER 10 g/100 g; TOCOPHEROL 15 g/100 g
INACTIVE INGREDIENTS: GLYCERIN 15 g/100 g; HYALURONIC ACID 30 g/100 g

ACTIVE INGREDIENTS

ALOE VERA LEAF、LONICERA JAPONICA FLOWER、TOCOPHEROL

PURPOSE

1. It can eradicate fungi and relieve onychomycosis, athlete's foot and othernail infections.

2. Able to penetrate nails, deeply repair damaged tissue, and promote healthy nail growth.

3. It can improve and nourish the nail bed, making your nails smoother.4. It uses mild ingredients and will not cause damage to your nails.

USES

1. Soak your nails in warm water to soften them2. Take an appropriate amount of this product and apply it evenly on the nails and periungual skin.3. Wait 2-3 minutes for it to be fully absorbed.

WARNING

Please keep out of reach of children. Do not swallow.Please clean your hands before use to ensure the best results from the product. Discontinue use if signs of irritation or rash occur. Store in a cool and dry place.

STOP USE

Discontinue use if signs of irritation or rash occur.

DO NOT USE

Discontinue use if signs of irritation or rash occur.

STORAGE AND HANDLING

Store in a cool and dry place.

KEEP OUT OF REACH OF CHILDREN

Please keep out of reach of children. Do not swallow.

INACTIVE INGREDIENT

GLYCERIN、HYALURONIC ACID